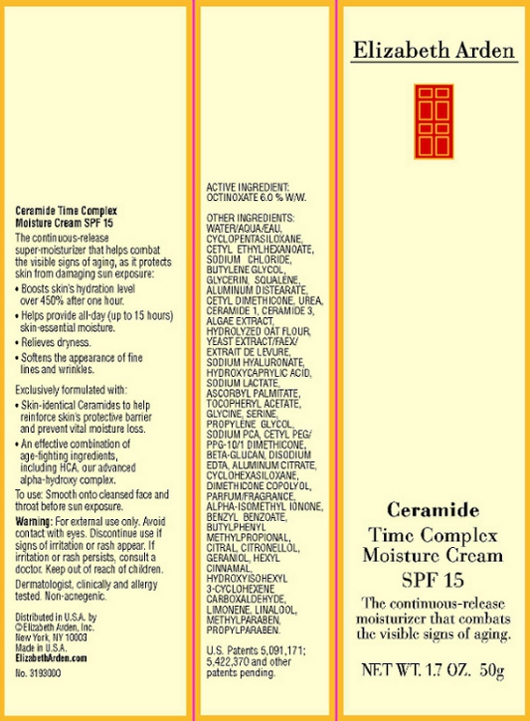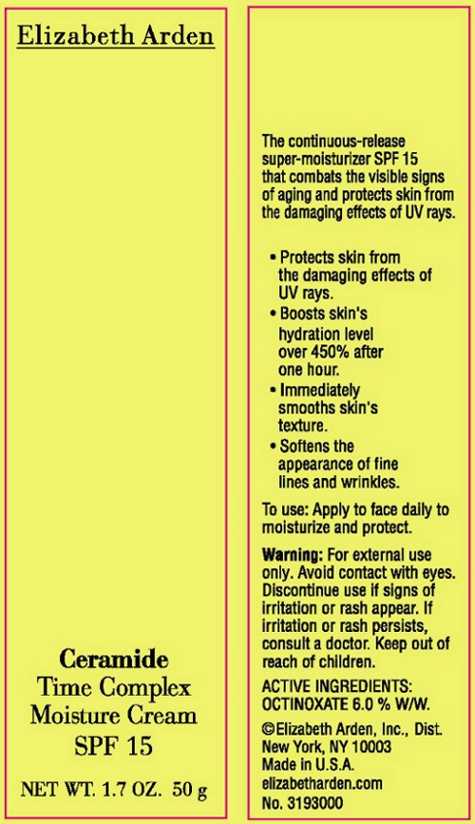 DRUG LABEL: Ceramide Time Complex Moisture Cream SPF 15
NDC: 67938-0732 | Form: CREAM
Manufacturer: Elizabeth Arden, Inc
Category: otc | Type: HUMAN OTC DRUG LABEL
Date: 20110601

ACTIVE INGREDIENTS: OCTINOXATE 3 g/50 g
INACTIVE INGREDIENTS: WATER; CYCLOMETHICONE 5; CETYL ETHYLHEXANOATE; SODIUM CHLORIDE; BUTYLENE GLYCOL; GLYCERIN; SQUALENE; ALUMINUM DISTEARATE; UREA; SODIUM LACTATE; GLYCINE; METHYLPARABEN; SODIUM PYRROLIDONE CARBOXYLATE; PROPYLENE GLYCOL; CERAMIDE 3; EDETATE DISODIUM; PROPYLPARABEN; CYCLOMETHICONE 6; ASCORBYL PALMITATE; SERINE; OAT BRAN; HYALURONATE SODIUM

BC0732

DESCRIPTION

The continuous-release super-moisturizer that helps combat visible signs of aging, as it protects skin from damaging sun exposure: Boosts skin's hydration level over 450% after one hour. Helps provide all-day (up to 15 hours) skin-essential moisture. Relieves dryness. Softens the appearance of fine lines and wrinkles. Exclusively formulated with: Skin-identical Ceramides to help reinforce skin's protective barrier and prevent vital moisture loss. An effective combination of age-fighting ingredients including HCA, our advanced alpha-hydroxy complex.

INDICATIONS & USAGE

To Use: Smooth on to cleansed face and throat before sun exposure.

WARNINGS

Warning: For external use only. Avoid contact with eyes. Discontinue use if signs of irritation or rash appear. If irritation or rash persists, consult a doctor. Keep out of reach of children.

OTC - ACTIVE INGREDIENT

Active Ingredient: Octinoxate 6% w/w.

INACTIVE INGREDIENT

Other Ingredients: Water/Aqua/Eau, Cyclopentasiloxane, Cetyl Ethylhexanoate, Sodium Chloride, Butylene Glycol, Glycerin, Squalene, Aluminum Distearate, Cetyl Dimethicone Urea, Ceramide 1, Ceramide 3, Algae Extract, Hydrolyzed Oat Flour, Yeast Extract/Faex/Extrait de Levure, Sodium Hyaluronate, Hydroxycaprylic Acid, Sodium Lactate, Ascorbyl Plamitate, Tocopheryl Acetate, Glycine, Serine, Propylene Glycol, Sodium PCA, Cetyl PEG/PPG-10/1 Dimethicone, Beta-Glucan, Disodium Edta, Aluminum Citrate, Cyclohexasiloxane, Dimethicone Copolyol, Parfum/Fragrance, Alpha-Isomethyl Ionone, Benzyl Benzoate, Betylpheny Methylpropional, Citral Citronellol, Geraniol, Hexyl Cinnamal, Hydroxyisohexyl 3-Cyclohexen, Carboxaldehyde, Limonene, Linalool, Methylparaben, Propylparaben.

DOSAGE & ADMINISTRATION

Smooth on to face and throat.

OTC - KEEP OUT OF REACH OF CHILDREN

Keep out of reach of children.

OTC - PURPOSE

Provides SPF 15 sun protection.

OTC - WHEN USING

Avoid contact with eyes.